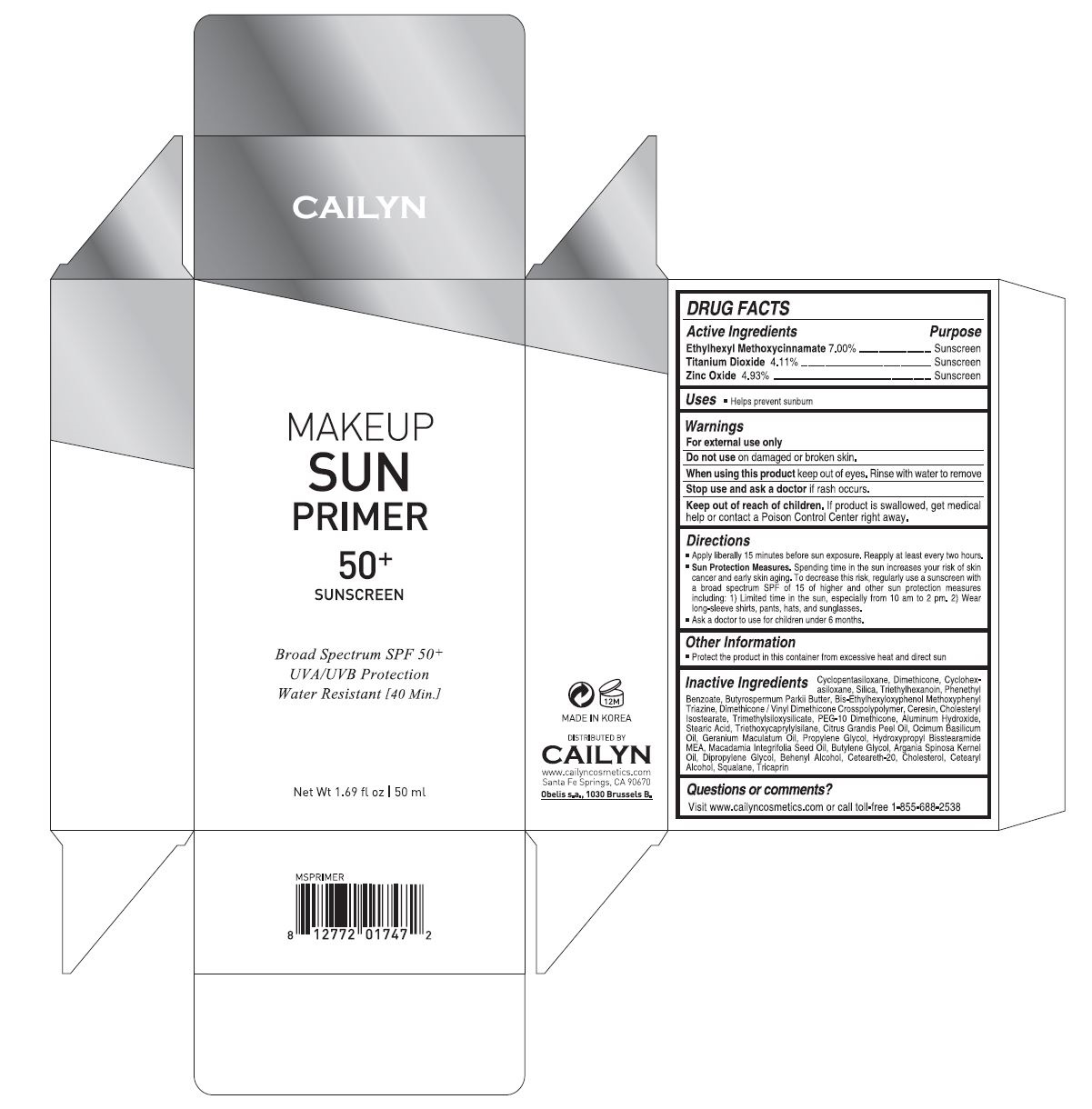 DRUG LABEL: MAKEUP SUN PRIMER
NDC: 70117-001 | Form: CREAM
Manufacturer: STW ENTERPRISE INC.
Category: otc | Type: HUMAN OTC DRUG LABEL
Date: 20151208

ACTIVE INGREDIENTS: OCTINOXATE 3.5 mg/50 mL; ZINC OXIDE 2.47 mg/50 mL; TITANIUM DIOXIDE 2.06 mg/50 mL
INACTIVE INGREDIENTS: CYCLOMETHICONE 5; DIMETHICONE; CYCLOMETHICONE 6; SILICON DIOXIDE; TRIETHYLHEXANOIN; PHENETHYL BENZOATE; SHEA BUTTER; BEMOTRIZINOL; DIMETHICONE/VINYL DIMETHICONE CROSSPOLYMER (HARD PARTICLE); CERESIN; CHOLESTERYL ISOSTEARATE; TRIMETHYLSILOXYSILICATE (M/Q 0.6-0.8); PEG-10 DIMETHICONE (600 CST); ALUMINUM HYDROXIDE; STEARIC ACID; TRIETHOXYCAPRYLYLSILANE; CITRUS MAXIMA FRUIT RIND OIL; BASIL OIL; GERANIUM MACULATUM ROOT OIL; PROPYLENE GLYCOL; HYDROXYPROPYL BISSTEARAMIDE MONOETHANOLAMIDE; MACADAMIA OIL; BUTYLENE GLYCOL; ARGAN OIL; DIPROPYLENE GLYCOL; DOCOSANOL; POLYOXYL 20 CETOSTEARYL ETHER; CHOLESTEROL; CETOSTEARYL ALCOHOL; SQUALANE; TRICAPRIN

Drug Facts

ACTIVE INGREDIENT

Ethylhexyl Methoxycinnamate 7.00%
Titanium Dioxide 4.11%
Zinc Oxide 4.93%

PURPOSE

Sunscreen

INDICATIONS AND USAGE

Helps prevent sunburn

DOSAGE AND ADMINISTRATION

Apply liberally 15 minutes before sun exposure. Reapply at least every two hours

Sun protection measures. Spending time in the sun increases your risk of skin cancer and early skin aging. To decrease this risk, regularly use a sunscreen with a broad spectrum SPF of 15 of higher and other sun protection measures including: 1) Limited time in the sun, especially from 10 am to 2 pm. 2) Wear long-sleeve shirts, pants, hats, and sunglasses
Ask a doctor to use for children under 6 months

WARNINGS

For external use only.
Do not use on damaged or broken skin.
When using this product, keep out of eyes. Rinse with water to remove.
Stop using and ask a doctor if rash occurs.

KEEP OUT OF REACH OF CHILDREN

Keep out of reach of the children. If product is swallowed, get medical help or contact a poison control center right away.

INACTIVE INGREDIENT

Cyclopentasiloxane, Dimethicone, Cyclohexasiloxane, Silica, Triethylhexanoin, Phenethyl Benzoate, Butyrospermum Parkii (Shea) Butter, Bis-Ethylhexyloxyphenol MethoxyphenylTriazine, Dimethicone/Vinyl Dimethicone Crosspolymer, Ceresin, Cholesteryl Isostearate, Trimethylsiloxysilicate, PEG-10 Dimethicone, Aluminum Hydroxide, Stearic Acid, Triethoxycaprylylsilane, Citrus Grandis (Grapefruit) Peel Oil, Ocimum Basilicum (Basil) Oil, Geranium Maculatum Oil, Propylene Glycol, Hydroxypropyl Bisstearamide MEA, Macadamia Integrifolia Seed Oil, Butylene Glycol, Argania Spinosa Kernel Oil, Dipropylene Glycol, Behenyl Alcohol, Ceteareth-20, Cholesterol, Cetearyl Alcohol, Squalane, Tricaprin